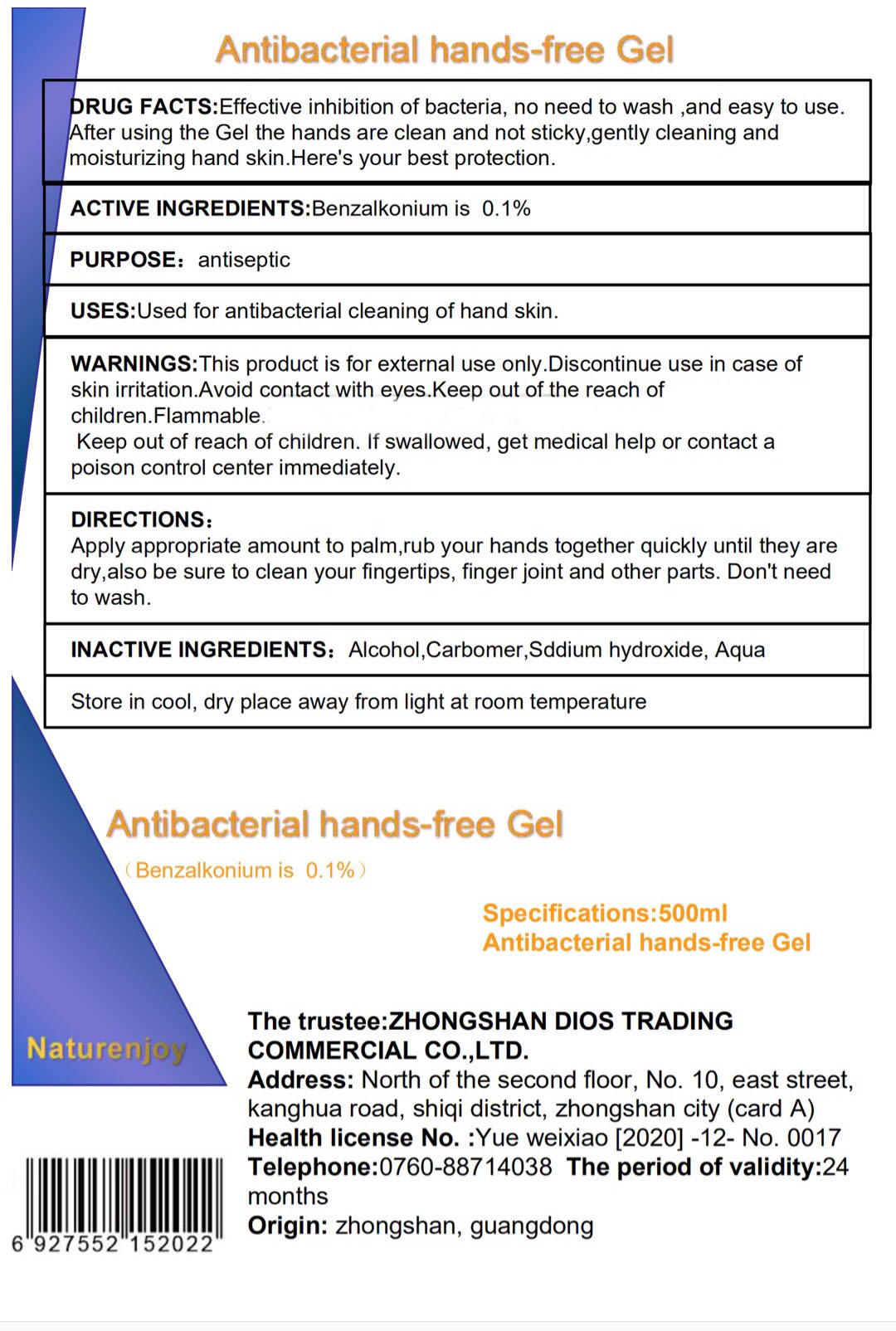 DRUG LABEL: Antibacterial Hand Free
NDC: 74532-002 | Form: GEL
Manufacturer: ZHONGSHAN DIOS TRADING COMMERCIAL CO., LTD.
Category: otc | Type: HUMAN OTC DRUG LABEL
Date: 20200406

ACTIVE INGREDIENTS: BENZALKONIUM CHLORIDE 0.1 g/100 mL
INACTIVE INGREDIENTS: ALCOHOL; WATER; CARBOMER 934; SODIUM HYDROXIDE

Drug Fact

Active Ingredient(s)

BENZALKONIUM CHLORIDE: 0.1%

Purpose

Antiseptic

Use

Use: Used for antibacterial cleaning of hand skin

Warnings

Warning: For external use only. Discontinue use if skin irritation occurs. Avoid contact with eyes. Flammable. Keep away from fire source

Keep out of reach of children. If swallowed, get medical help or contact a Poison Control Center immeidately.

DOSAGE AND ADMINISTRATION

Directions: Apply appropriate amount to plams, rub your hands quickly untill they are dry. Also be sure to clean your finger tips, finger joints and other parts. Don't need to wash

Inactive ingredients

Inactive Ingredients: Alcohol, Water, Carbomer, Sodium Hydroxide

STORAGE AND HANDLING

Storage: Store in cool dry place away from light at room temperature